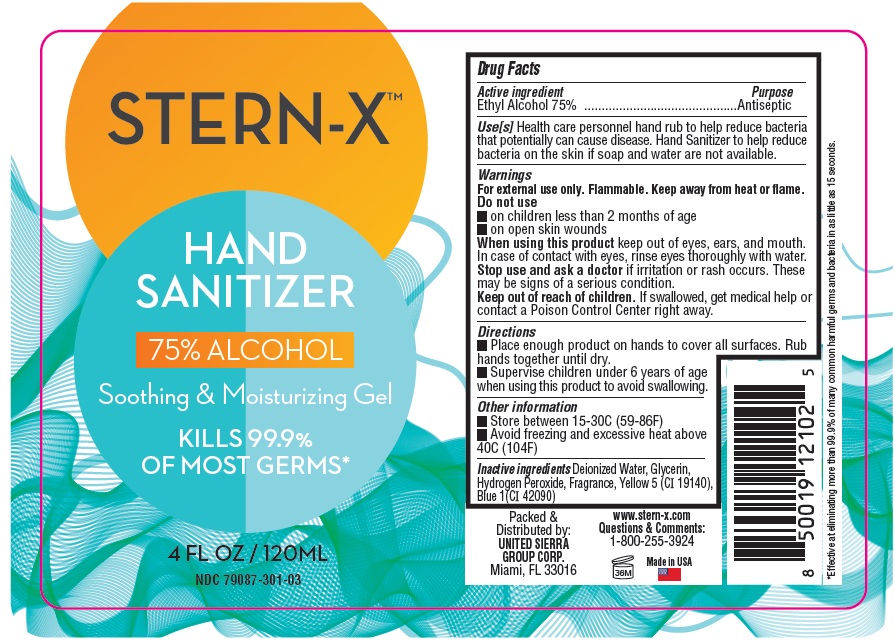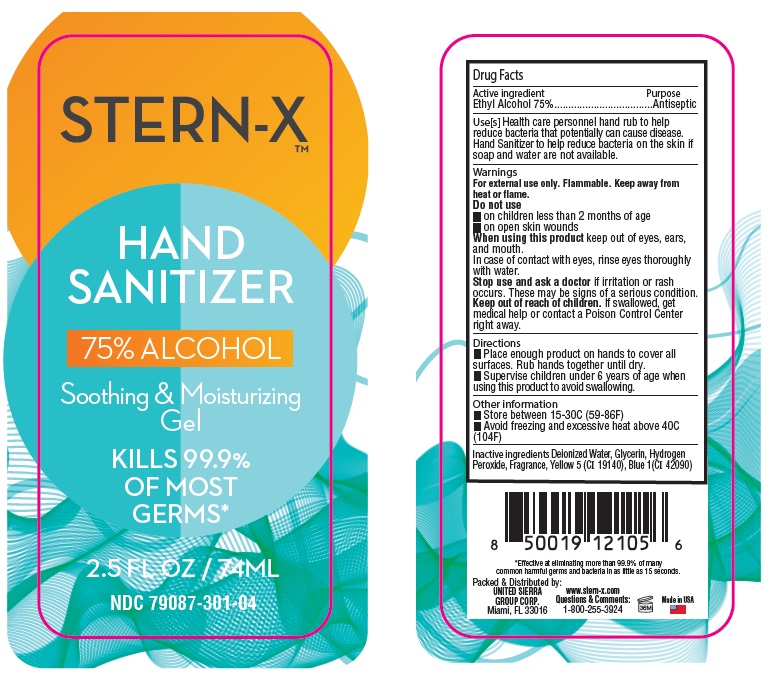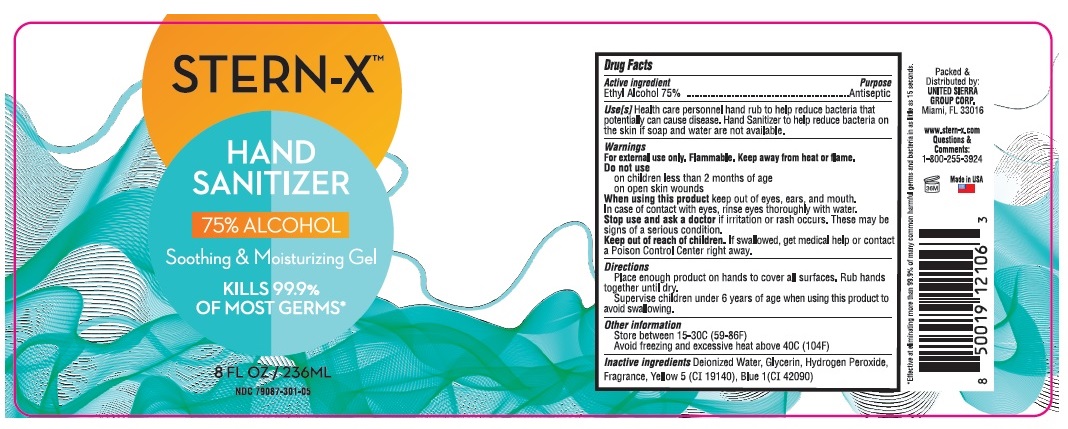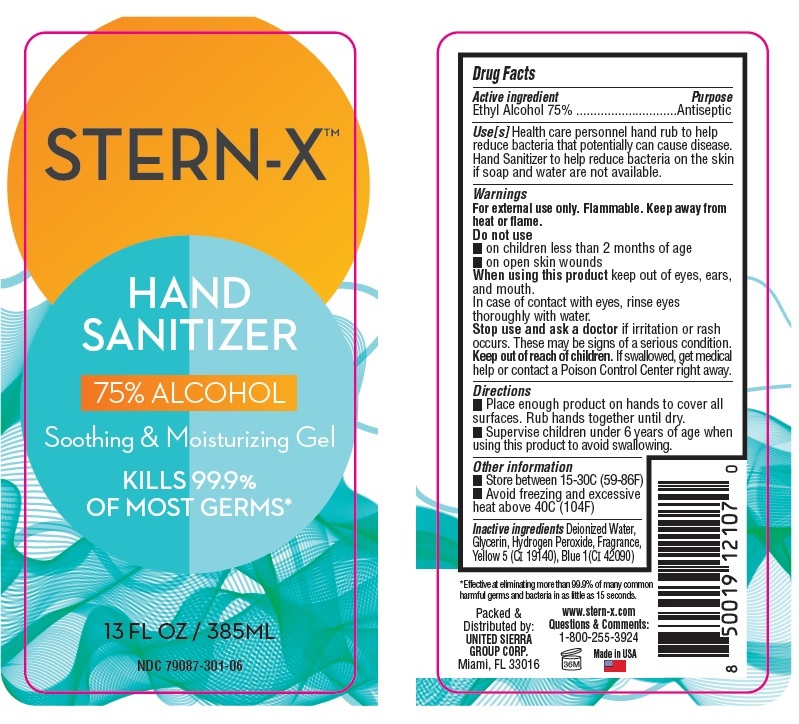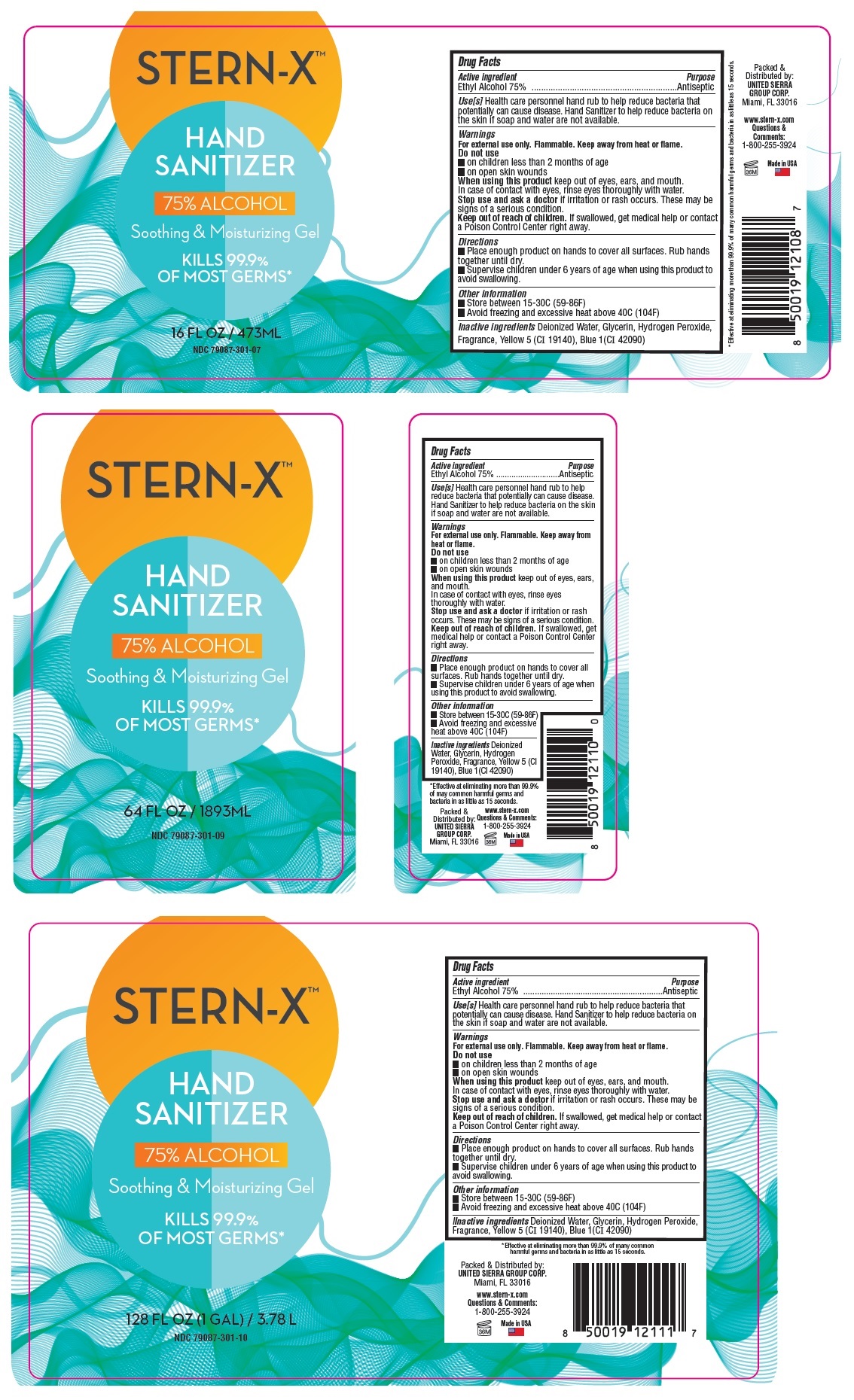 DRUG LABEL: STERN-X HAND SANITIZER
NDC: 79087-301 | Form: GEL
Manufacturer: United Sierra Group Corp
Category: otc | Type: HUMAN OTC DRUG LABEL
Date: 20210405

ACTIVE INGREDIENTS: ALCOHOL 75 mL/100 mL
INACTIVE INGREDIENTS: WATER; GLYCERIN; HYDROGEN PEROXIDE; FD&C YELLOW NO. 5; FD&C BLUE NO. 1

STERN-X™ HAND SANITIZER

Active ingredient

Ethyl Alcohol 75%

Purpose

Antiseptic

Use[s]

Health care personnel hand rub to help reduce bacteria that potentially can cause disease. Hand Sanitizer to help reduce bacteria on the skin if soap and water are not available.

Warnings

For external use only. Flammable. Keep away from heat or flame.

Do not use

- on children less than 2 months of age
- on open skin wounds

When using this product keep out of eyes, ears, and mouth. In case of contact with eyes, rinse eyes thoroughly with water.

Stop use and ask a doctor if irritation or rash occurs. These may be signs of a serious condition.

Keep out of reach of children. If swallowed, get medical help or contact a Poison Control Center right away.

Directions

- Place enough product on hands to cover all surfaces. Rub hands together until dry.
- Supervise children under 6 years of age when using this product to avoid swallowing.

Other information

- Store between 15-30C (59-86F)
- Avoid freezing and excessive heat above 40C (104F)

Inactive ingredients

Deionized Water, Glycerin, Hydrogen Peroxide, Fragrance, Yellow 5 (CI 19140), Blue 1(CI 42090)

Soothing & Moisturizing Gel

KILLS 99.9% OF MOST GERMS*

Packed & Distributed by:
UNITED SIERRA GROUP CORP.
Miami, FL 33016

www.stern-x.com

Questions & Comments:1-800-255-3924

Made in USA

*Effective at eliminating more than 99.9% of many common harmful germs and bacteria in as little as 15 seconds.